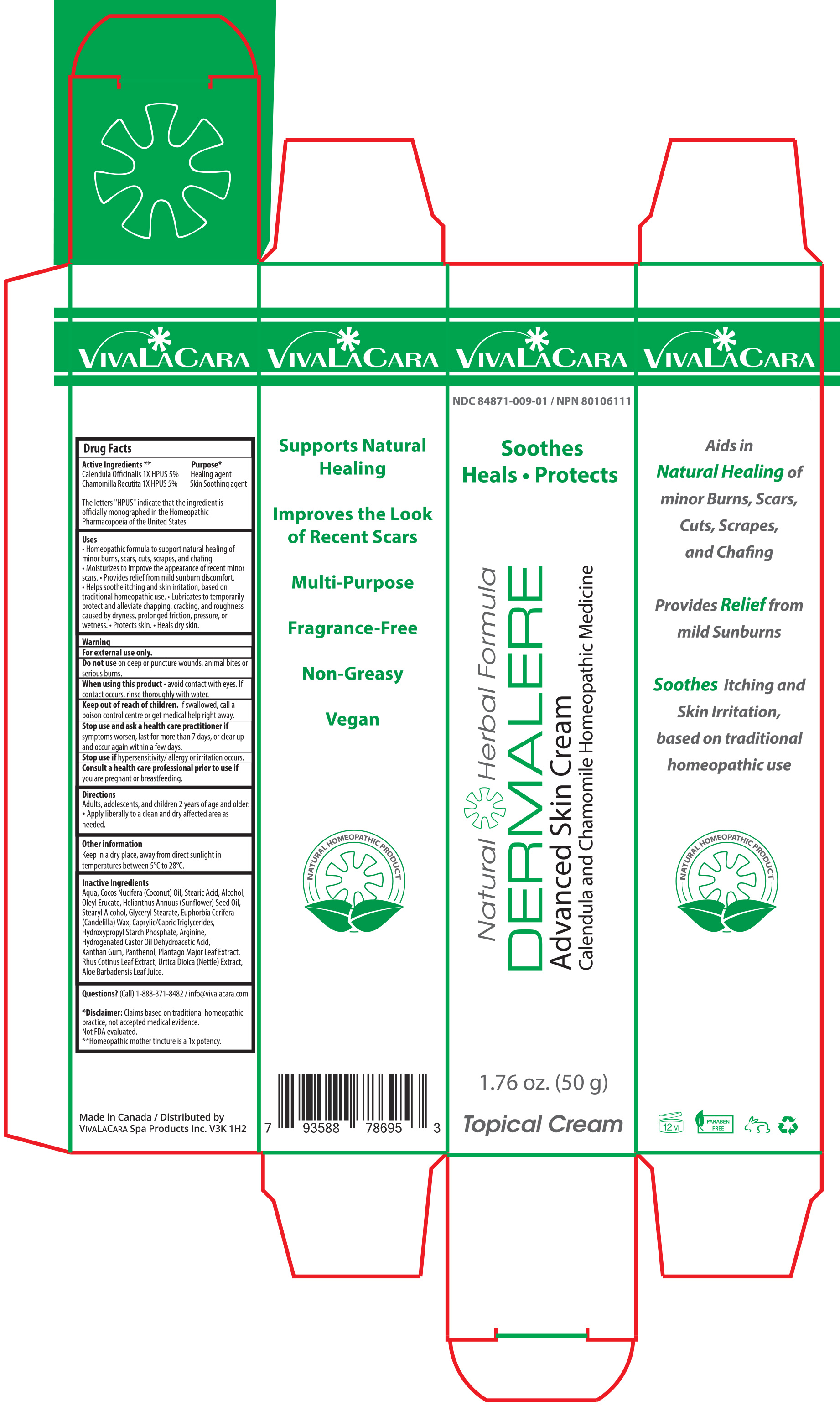 DRUG LABEL: VivaLaCara Dermalere Advanced Skin Cream
NDC: 84871-009 | Form: CREAM
Manufacturer: VivaLaCara Spa Products Inc.
Category: homeopathic | Type: HUMAN OTC DRUG LABEL
Date: 20250120

ACTIVE INGREDIENTS: CALENDULA OFFICINALIS FLOWER 5 g/100 g; CHAMOMILE 5 g/100 g
INACTIVE INGREDIENTS: COCOS NUCIFERA (COCONUT) OIL; AQUA; STEARYL ALCOHOL; XANTHAN GUM; ARGININE; HYDROGENATED CASTOR OIL; STEARIC ACID; HELIANTHUS ANNUUS (SUNFLOWER) SEED OIL; GLYCERYL MONOSTEARATE; URTICA DIOICA LEAF; COTINUS COGGYGRIA LEAF; DEXPANTHENOL; EUPHORBIA CERIFERA (CANDELILLA) WAX; CAPRYLIC/CAPRIC TRIGLYCERIDE; DEHYDROACETIC ACID; ALOE VERA LEAF; OLEYL ERUCATE; ALCOHOL; PLANTAGO MAJOR LEAF; STARCH, CORN

Active Ingredient Section

Calendula Officinalis 1X HPUS 5%

Chamomilla Recutita 1X HPUS 5%

The letters "HPUS" indicate that the ingredient is officially monographed in the Homeopathic Pharmacopoeia of the United States.

Purpose

Healing and Skin Soothing

Uses

•Homeopathic formula to support natural healing of minor burns, scars, cuts, scrapes, and chafing.

• Moisturizes to improve the appearance of recent minor scars.

• Provides relief from mild sunburn discomfort.

• Helps soothe itching and skin irritation, based on traditional homeopathic use.

• Lubricates to temporarily protect and alleviate chapping, cracking, and roughness caused by dryness, prolonged friction, pressure, or wetness.

• Protects skin.

• Heals dry skin.

Warning

For external use only.

Do not use on deep or puncture wounds, animal bites or serious burns.

When using

When using this product • avoid contact with eyes. If contact occurs, rinse thoroughly with water.

Keep out of reach of children. If swallowed, call a poison control centre or get medical help right away.

Stop use

Stop use and ask a health care practitioner if symptoms worsen, last for more than 7 days, or clear up and occur again within a few days.

Stop use if hypersensitivity/ allergy or irritation occurs.

Pregnancy or breast feeding

Consult a health care professional prior to use if you are pregnant or breastfeeding.

Directions

Adults, adolescents, and children 2 years of age and older: •Apply liberally to a clean and dry affected area as needed.

Other information

Keep in a dry place, away from direct sunlight in temperatures between 5°C to 28°C.

Inactive ingredient section

Aqua, Cocos Nucifera (Coconut) Oil, Stearic Acid, Alcohol, Oleyl Erucate, Helianthus Annuus (Sunflower) Seed Oil, Stearyl Alcohol, Glyceryl Stearate, Euphorbia Cerifera (Candelilla) Wax, Caprylic/Capric Triglycerides, Hydroxypropyl Starch Phosphate, Arginine, Hydrogenated Castor Oil Dehydroacetic Acid, Xanthan Gum, Panthenol, Plantago Major Leaf Extract, Rhus Cotinus Leaf Extract, Urtica Dioica (Nettle) Extract, Aloe Barbadensis Leaf Juice.

Questions and Disclaimer

Questions? (Call) 1-888-371-8482 / info@vivalacara.com

* Disclaimer: Claims based on traditional homeopathic practice, not accepted medical evidence. Not FDA evaluated.

**Homeopathic mother tincture is a 1x potency.

PACKAGE LABEL

VivaLaCara Logo NDC 84871-006-02 / NPN 80106111

Natural Herbal Formula

DERMALERE

Advanced Skin Cream

Calendula and Chamomile Homeopathic Medicine

Soothes • Heals • Protects

1.76 oz. (50 g)

Topical Cream